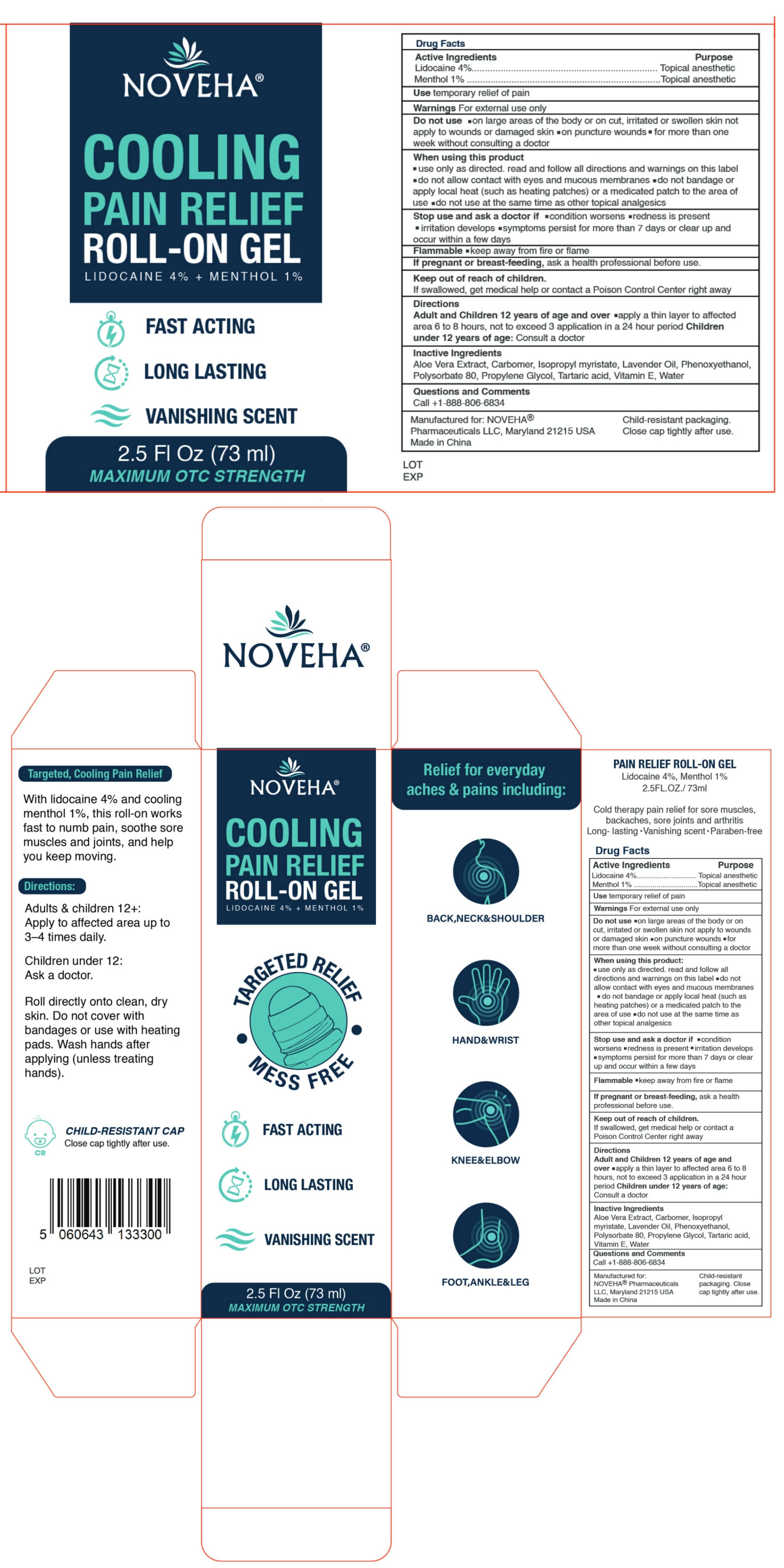 DRUG LABEL: Pain Relief Gel-Roll On
NDC: 84008-002 | Form: GEL
Manufacturer: Bullet point LLC
Category: otc | Type: HUMAN OTC DRUG LABEL
Date: 20251104

ACTIVE INGREDIENTS: LIDOCAINE 0.04 g/1 mL; MENTHOL 0.01 g/1 mL
INACTIVE INGREDIENTS: WATER; PROPYLENE GLYCOL; TARTARIC ACID; POLYACRYLIC ACID (250000 MW); PHENOXYETHANOL; ISOPROPYL MYRISTATE; ALOE VERA LEAF; LAVENDER OIL; .ALPHA.-TOCOPHEROL, D-; POLYSORBATE 80

Active Ingredient

Lidocaine 4.0% (w/w ...... Purpose: Topical Anesthetic)

Menthol 1.0% (w/w ...... Purpose: Topical Analgesic)

Purpose

(Lidocaine) Topical Anesthetic

(Menthol) Topical Analgesic

Warnings

For external use only

Use

Temporary relief of pain

Do not use

• On large areas of the body or on cut, irritated, or swollen skin not apply to wounds or damaged skin • on puncture wounds • for more than one week without consulting a doctor.

When using this product

• Use only as directed. Read and follow all directions and warnings on this label

• Do not allow contact with eyes and mucous membranes

• Do not bandage or apply local heat (such as heating patches) or a medicated patch to the area of use

• Do not use at the same time as other topical analgesics

Stop use if

• Condition worsens

• Redness is present

• Irritation develops

• Symptoms persist for more than 7 days or clear up and occur within a few days

Ask a doctor if

• Condition worsens

• Redness is present

• Irritation develops

• Symptoms persist for more than 7 days or clear up and occur within a few days

WARNINGS AND PRECAUTIONS

Flammable

• Keep away from fire or flame

If pregnant or breast-feeding

- Ask a health professional before use

Keep out of reach of children

If swallowed, get medical help or contact the Poison Control Center right away

Directions

Adults and children 12 years of age and over:

- Apply a thin layer to the affected area for 6 to 8 hours
- Not to exceed 3 applications in a 24 hour period

Children under 12 years old: Consult a doctor

Inactive Ingredients
Aloe Vera Extract, Carbomer, Isopropyl myristate, Lavender Oil, Phenoxyethanol, Polysorbate 80, Propylene Glycol, Tartaric acid, Vitamin E, Water

OTHER SAFETY INFORMATION

Child-resistant packaging. Close the cap tightly after use.